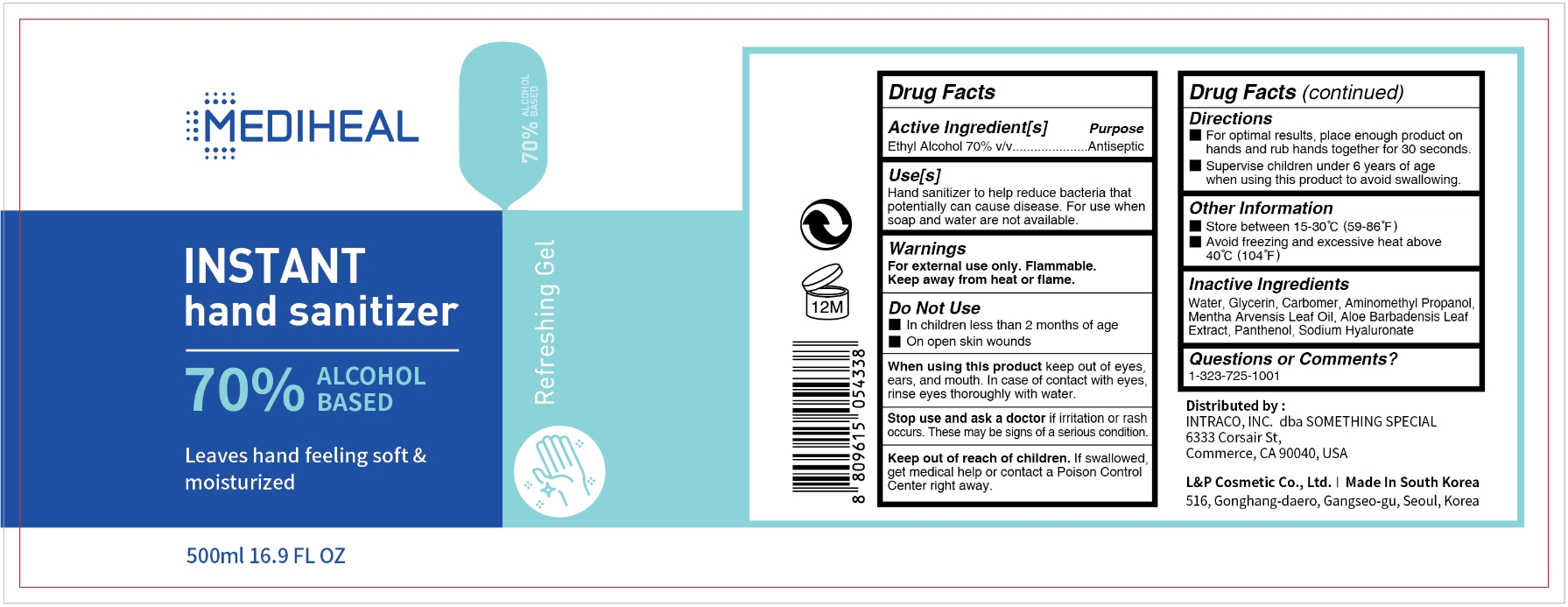 DRUG LABEL: Mediheal Insant Hand Sanitizer 70% 500ml
NDC: 74005-030 | Form: GEL
Manufacturer: L&P Cosmetic Co., Ltd.
Category: otc | Type: HUMAN OTC DRUG LABEL
Date: 20200521

ACTIVE INGREDIENTS: ALCOHOL 70 mL/100 mL
INACTIVE INGREDIENTS: PANTHENOL; CARBOMER 940; HYALURONATE SODIUM; WATER; AMINOMETHYLPROPANOL; MENTHA ARVENSIS LEAF OIL; GLYCERIN; ALOE VERA LEAF

MEDIHEAL INSTANT HAND SANITIZER 70% 500ml

Active Ingredient(s)

Ethyl Alcohol 70% v/v. Purpose: Antiseptic

Purpose

Antiseptic, Hand Sanitizer

Use

Hand sanitizer to help reduce bacteria that potentially can cause disease. For use when soap and water are not available.

Warnings

For external use only. Flammable.

Keep away from heat or flame

Do not use

- In children less than 2 months of age
- On open skin wounds

When using this product keep out of eyes, ears, and mouth. In case of contact with eyes, rinse eyes thoroughly with water.

Stop use and ask a doctor if irritation or rash occurs. These may be signs of a serious condition.

Keep out of reach of children. If swallowed, get medical help or contact a Poison Control Center right away.

Directions

▪ For optimal results, place enough product on hands and rub hands together for 30 seconeds.
▪ Supervise children under 6 years of age when using this product to avoid swallowing.

Other information

- Store between 15-30C (59-86F)
- Avoid freezing and excessive heat above 40C (104F)

Inactive ingredients

Water, Glycerin, Carbomer, Aminomethyl Propanol, Mentha Arvensis Leaf Oil, Aloe Barbadensis Leaf Extract, Panthenol, Sodium Hyaluronate

Questions or Comments?

1-323-725-1001

Package Label - Principal Display Panel

MEDIHEAL
INSTANT
hand sanitizer
70% ALCOHOL BASED
Leaves hand feeling soft
& moisturized
Refreshing Gel
500ml 16.9 FL OZ